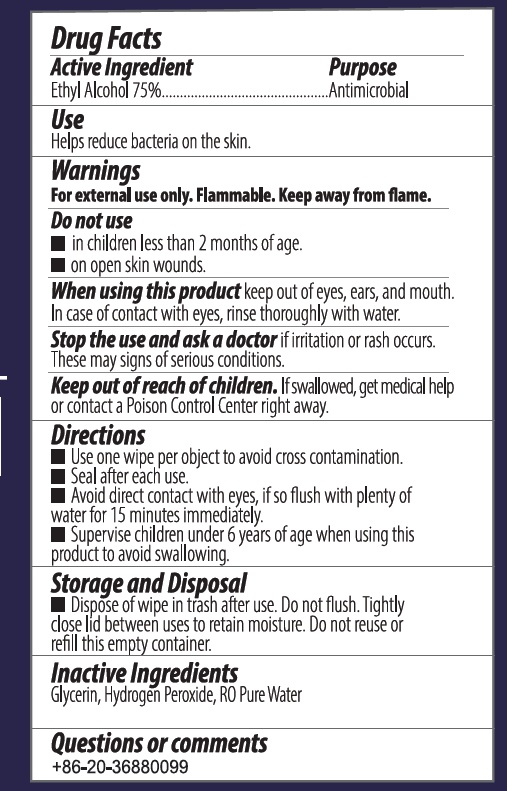 DRUG LABEL: Disinfectant Wipes
NDC: 79600-001 | Form: SWAB
Manufacturer: GUANGZHOU DICALLO CO.,LTD
Category: otc | Type: HUMAN OTC DRUG LABEL
Date: 20201030

ACTIVE INGREDIENTS: ALCOHOL 75 1/100 1
INACTIVE INGREDIENTS: WATER; HYDROGEN PEROXIDE; GLYCERIN

DOSAGE AND ADMINISTRATION

Use one wipe per object to avoid cross contamination.

Seal after each use.

Avoid direct contact with eyes, if so flush with plenty if water for 15 minutes immediately.

Supervise children under 6 years of age when using this product to avoid swallowing.

INACTIVE INGREDIENT

Gylcerin, Hydrogen Proxide, Ro Pure Water

ACTIVE INGREDIENT

Ethyl Alcohol 75%…………Antimicriobial

WARNINGS

For external use only. Flammable. Keep away from flame.

ASK DOCTOR

Stop the use and ask a doctor if irritation or rash occurs. These may signs if serious conditions.

KEEP OUT OF REACH OF CHILDREN

If swalloerd, get medical help or contact a Poison Control Center right away.

Do not use

- in child less than 2 months of age.
- on open skin wounds.

When using this product, keep out od eyes, ears, and mouth. In case of contact with eyes, rinse thoroughly with water.

INDICATIONS AND USAGE

Helps reduce bacteria on the skin.

PURPOSE

Helpa reduce bacrteria on the skin.